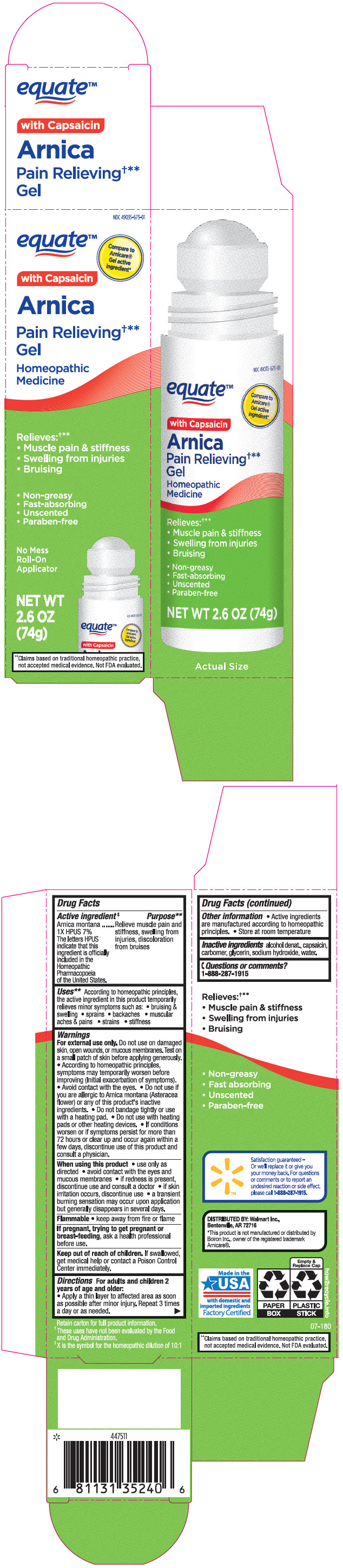 DRUG LABEL: Equate Arnica Pain Relieving
NDC: 49035-673 | Form: GEL
Manufacturer: Wal-Mart Stores, Inc.
Category: homeopathic | Type: HUMAN OTC DRUG LABEL
Date: 20220113

ACTIVE INGREDIENTS: ARNICA MONTANA WHOLE 70 mg/1 g
INACTIVE INGREDIENTS: SODIUM LAURETH-3 SULFATE; CAPSAICIN; CARBOMER HOMOPOLYMER, UNSPECIFIED TYPE; GLYCERIN; SODIUM HYDROXIDE; WATER

Equate™ Arnica Pain Relieving†** Gel

Drug Facts

Active ingredient‡

Arnica Montana 1X HPUS 7%
The letters HPUS indicate that this ingredient is officially included in the Homeopathic Pharmacopoeia of the United States.

Purpose**

Relieve muscle pain and stiffness, swelling from injuries, discoloration from bruises

Uses**

According to homeopathic principles, the active ingredient in this product temporarily relieves minor symptoms such as:

- bruising and swelling
- sprains
- backaches
- muscular aches and pains
- strains
- stiffness

Warnings

For external use only. Do not use on damaged skin, open wounds, or mucous membranes. Test on a small patch of skin before applying generously.

- According to homeopathic principles, symptoms may temporarily worsen before improving (Initial exacerbation of symptoms).
- Avoid contact with eyes.
- Do not use if you are allergic to Arnica montana (Asteracea flower) or any of this product's inactive ingredients.
- Do not bandage tightly or use with a heating pad.
- Do not use with heating pads or other heating devices.
- If conditions worsen or if symptoms persist for more than 72 hours or clear up and occur again within a few days, discontinue use of this product and consult a physician.

When using this product

- use only as directed
- avoid contact with eyes and mucous membranes
- if redness is present, discontinue use and consult a doctor
- if skin irritation occurs, discontinue use
- a transient burning sensation may occur upon application but generally disappears in several days.

Flammable

- keep away from fire or flame

PREGNANCY OR BREAST FEEDING

If pregnant, trying to get pregnant or breast-feeding, ask a health professional before use.

Keep out of reach of children. If swallowed, get medical help or contact a Poison Control Center immediately.

Directions

For adults and children 2 years of age and older:

- Apply a thin layer to affected area as soon as possible after minor injury. Repeat 3 times a day or as needed.

Other information

- Active ingredients are manufactured according to homeopathic principles.
- Store at room temperature

Inactive ingredients

alcohol denat., capsaicin, carbomer, glycerin, sodium hydroxide, water.

Questions or comments?

1-888-287-1915

DISTRIBUTED BY: Walmart Inc.,
Bentonville, AR 72716

† These uses have not been evaluated by the Food and Drug Administration.
‡ X is the symbol for the homeopathic dilution 10:1
** Claims based on traditional homeopathic practice, not accepted medical evidence. Not FDA evaluated.

PRINCIPAL DISPLAY PANEL - 74 g Cylinder Carton

NDC 49035-673-01

equate™

Compare to
Arnicare®
Gel active
ingredient*

with Capsaicin

Arnica

Pain Relieving†**
Gel

Homeopathic
Medicine

Relieves:†**

- Muscle pain & stiffness
- Swelling from injuries
- Bruising

- Non-greasy
- Fast-absorbing
- Unscented
- Paraben-free

No Mess
Roll-On
Applicator

NET WT
2.6 OZ
(74g)

**Claims based on traditional homeopathic practice,
not accepted medical evidence. Not FDA evaluated.